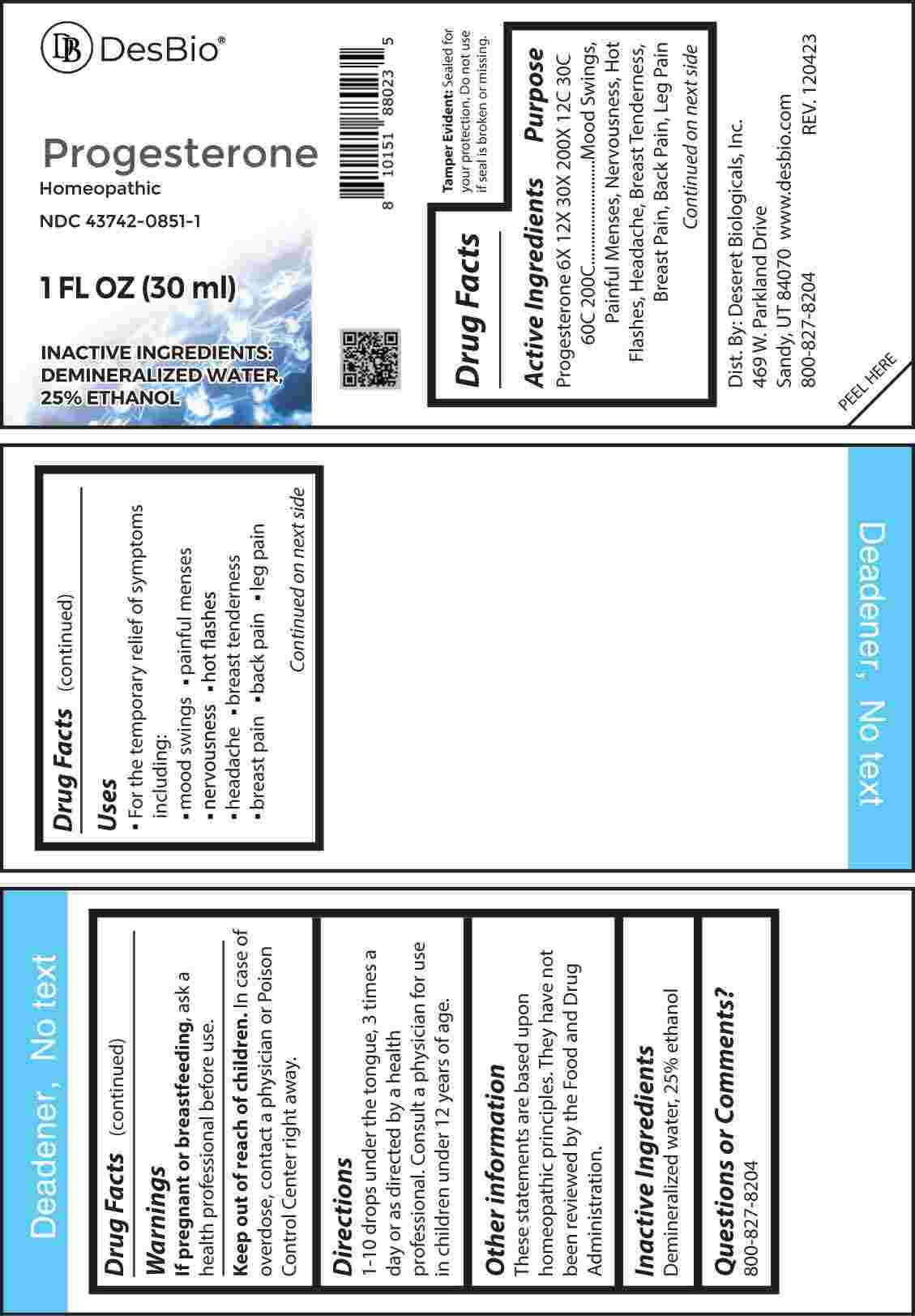 DRUG LABEL: Progesterone
NDC: 43742-0851 | Form: LIQUID
Manufacturer: Deseret Biologicals, Inc.
Category: homeopathic | Type: HUMAN OTC DRUG LABEL
Date: 20240314

ACTIVE INGREDIENTS: PROGESTERONE 6 [hp_X]/1 mL
INACTIVE INGREDIENTS: WATER; ALCOHOL

DRUG FACTS:

ACTIVE INGREDIENTS:

Progesterone 6X, 12X, 30X, 200X, 12C, 30C, 60C, 200C.

PURPOSE:

Progesterone - Mood Swings, Painful Menses, Nervousness, Hot Flashes, Headache, Breast Tenderness, Breast Pain, Back Pain, Leg Pain

USES:

• For the temporary relief of symptoms including:

• mood swings • painful menses • nervousness

• hot flashes • headache • breast tenderness

• breast pain • back pain • let pain

These statements are based upon homeopathic principles. They have not been reviewed by the Food and Drug Administration.

WARNINGS:

If pregnant or breast-feeding, seek advice of a health professional before use.

Keep out of reach of children. In case of overdose, contact a physician or Poison Control Center right away.

Tamper Evident: Sealed for your protection. Do not use if seal is broken or missing.

KEEP OUT OF REACH OF CHILDREN:

In case of overdose, contact a physician or Poison Control Center right away.

DIRECTIONS:

1-10 drops under the tongue, 3 times a day or as directed by a health professional. Consult a physician for use in children under 12 years of age.

INACTIVE INGREDIENTS:

Demineralized water, 25% ethanol

QUESTIONS:

Dist. By: Deseret Biologicals, Inc.

469 W. Parkland Drive

Sandy, UT 84070

www.desbio.com

800-827-8204

PACKAGE LABEL DISPLAY:

DesBio

Progesterone

Homeopathic

NDC 43742-0851-1

1 FL OZ (30 ml)